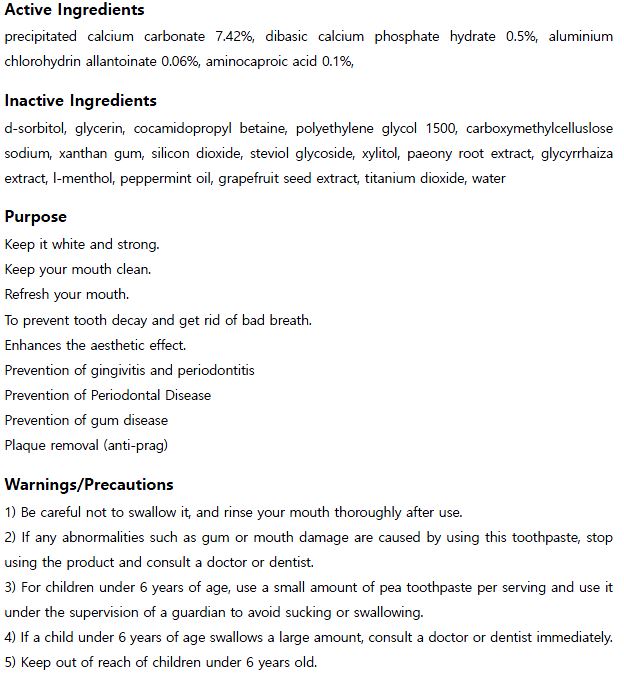 DRUG LABEL: HiMangChanToothpaste
NDC: 73065-0003 | Form: PASTE
Manufacturer: WOORILIFE&HEALTH
Category: otc | Type: HUMAN OTC DRUG LABEL
Date: 20210412

ACTIVE INGREDIENTS: AMINOCAPROIC ACID 0.1 g/100 g; DIBASIC CALCIUM PHOSPHATE DIHYDRATE 0.5 g/100 g; CALCIUM CARBONATE 7.42 g/100 g; ALCLOXA 0.06 g/100 g
INACTIVE INGREDIENTS: XYLITOL; LEVOMENTHOL

Woorilife&Health - HiMangChan Toothpaste

ACTIVE INGREDIENT

precipitated calcium carbonate, aminocaproic acid, aluminium chlorohydrin allantoinate, dibasic calcium phosphate hydrate

INACTIVE INGREDIENT

glycerin, xylitol, xanthan gum, water, l-menthol, etc

PURPOSE

Keep your teeth white and strong.
Keep your mouth clean.
Refresh your mouth.
To prevent tooth decay and get rid of bad breath.
Enhances the aesthetic effect.
Prevention of gingivitis and periodontitis
Prevention of Periodontal Disease
Prevention of gum disease
Plaque removal (anti-prag)

keep out of reach of the children

INDICATIONS AND USAGE

Apply an appropriate amount to toothbrush and brush your teeth

WARNINGS

1) Be careful not to swallow it, and rinse your mouth thoroughly after use.

2) If any abnormalities such as gum or mouth damage are caused by using this toothpaste, stop using the product and consult a doctor or dentist.

3) For children under 6 years of age, use a small amount of pea toothpaste per serving and use it under the supervision of a guardian to avoid sucking or swallowing.

4) If a child under 6 years of age swallows a large amount, consult a doctor or dentist immediately.

5) Keep out of reach of children under 6 years old.

DOSAGE AND ADMINISTRATION

for external use only